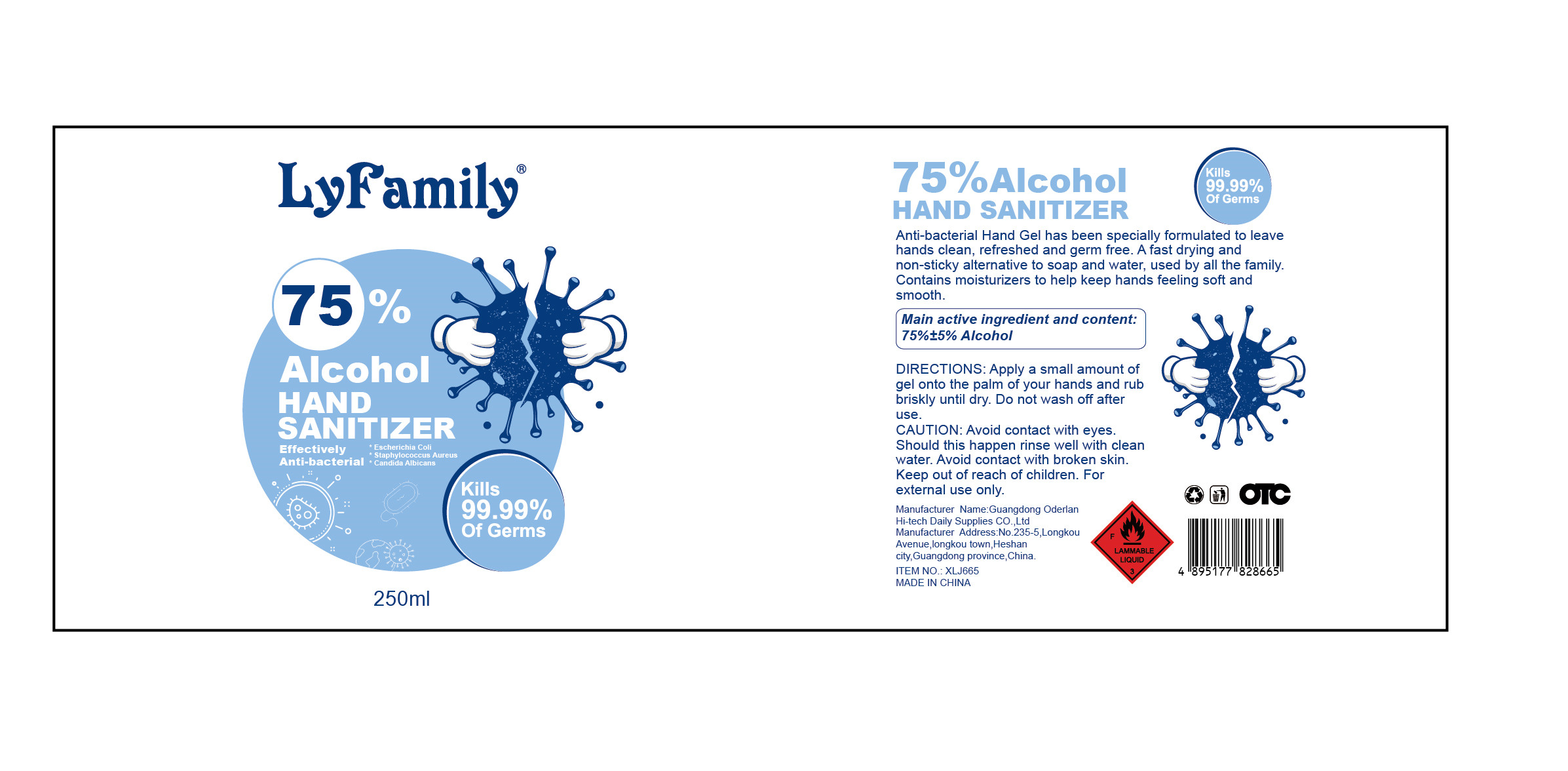 DRUG LABEL: LyFamily 75% Alcohol HAND SANITIZER
NDC: 40397-004 | Form: GEL
Manufacturer: Guangdong Oderlan Hi-Tech Daily Supplies Co., Ltd.
Category: otc | Type: HUMAN OTC DRUG LABEL
Date: 20200509

ACTIVE INGREDIENTS: ALCOHOL 187.5 mL/250 mL
INACTIVE INGREDIENTS: AMINOMETHYLPROPANOL; WATER; CARBOMER COPOLYMER TYPE A (ALLYL PENTAERYTHRITOL CROSSLINKED)

DOSAGE AND ADMINISTRATION

Keep away from fire or flame.

INACTIVE INGREDIENT

Carbomer

Aminomethyl Propanol

Deionized Water

INDICATIONS AND USAGE

Apply a small amount of gel onto the palm of your hands and rub briskly until dry. Do not wash off after use.

ACTIVE INGREDIENT

Alcohol

keep out of children

PURPOSE

Disinfection
Sterilization
No Rinseing

WARNINGS

Avoid contact with eyes. Should this happen rinse well with clean water. Avoid contact with broken skin. Keep out of reach
of children. For extermnal use only.